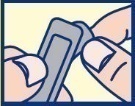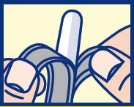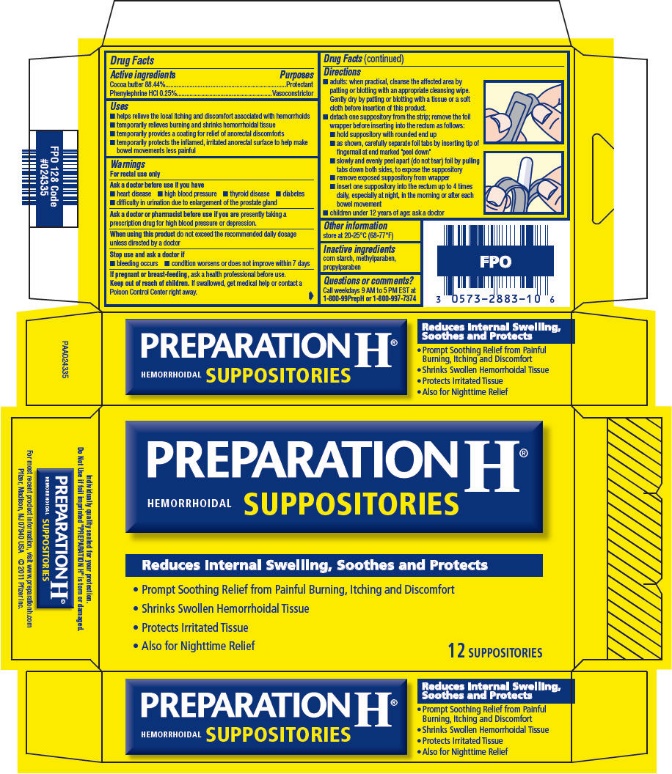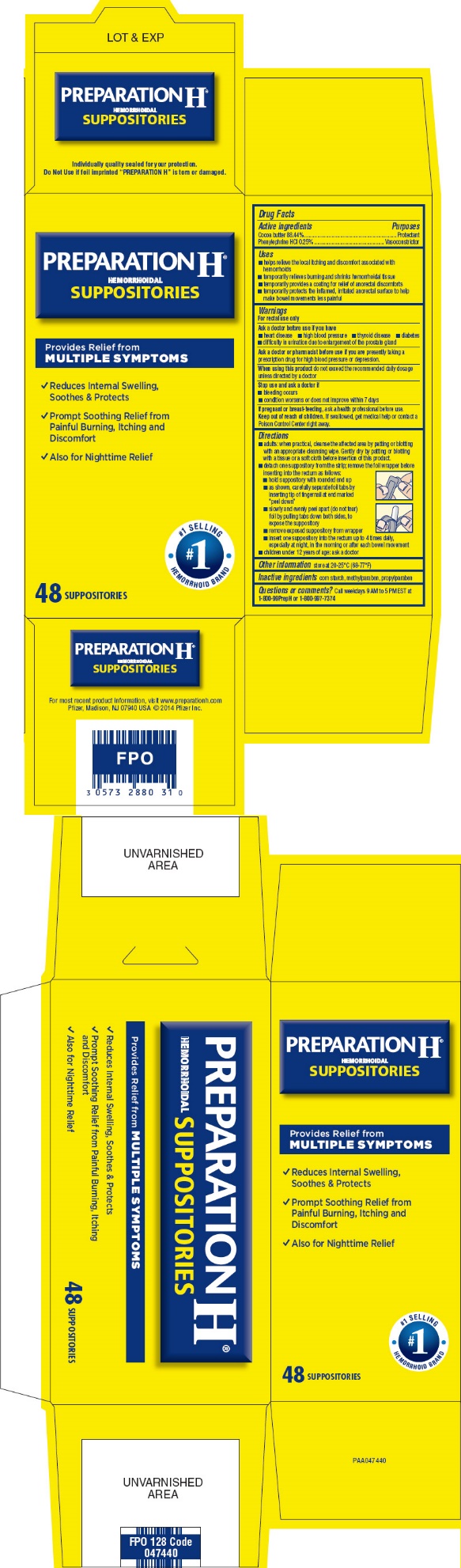 DRUG LABEL: PREPARATION H
NDC: 0573-2883 | Form: SUPPOSITORY
Manufacturer: Haleon US Holdings LLC
Category: otc | Type: HUMAN OTC DRUG LABEL
Date: 20240302

ACTIVE INGREDIENTS: COCOA BUTTER 2211 mg/1 1; PHENYLEPHRINE HYDROCHLORIDE 6.25 mg/1 1
INACTIVE INGREDIENTS: STARCH, CORN; METHYLPARABEN; PROPYLPARABEN

Drug Facts

Active Ingredients

Cocoa butter 88.44%

Phenylephrine HCl 0.25%

Purposes

Protectant

Vasoconstrictor

Uses

- helps relieve the local itching and discomfort associated with hemorrhoids
- temporarily relieves burning and shrinks hemorrhoidal tissue
- temporarily provides a coating for relief of anorectal discomforts
- temporarily protects the inflamed, irritated anorectal surface to help make bowel movements less painful

Warnings

For rectal use only

Ask a doctor before use if you have

- heart disease
- high blood pressure
- thyroid disease
- diabetes
- difficulty in urination due to enlargement of the prostate gland

Ask a doctor or pharmacist before use if you arepresently taking a prescription drug for high blood pressure or depression.

WHEN USING

When using this productdo not exceed the recommended daily dosage unless directed by a doctor

Stop use and ask a doctor if

- bleeding occurs
- condition worsens or does not improve within 7 days

PREGNANCY OR BREAST FEEDING

If pregnant or breast-feeding,ask a health professional before use.

Keep out of reach of children.If swallowed, get medical help or contact a Poison Control Center right away.

Directions

- adults: when practical, cleanse the affected area by patting or blotting with an appropriate cleansing wipe. Gently dry by patting or blotting with a tissue or a soft cloth before insertion of this product.
- detach one suppository from the strip; remove the foil wrapper before inserting into the rectum as follows:
  - hold suppository with rounded end up
  - as shown, carefully separate foil tabs by inserting tip of fingernail at end marked "peel down"
  - slowly and evenly peel apart (do not tear) foil by pulling tabs down both sides, to expose the suppository
  - remove exposed suppository from wrapper
  - insert one suppository into the rectum up to 4 times daily, especially at night, in the morning or after each bowel movement
- children under 12 years of age: ask a doctor

Other information

store at 20-25°C (68-77°F)

Inactive ingredients

corn starch, methylparaben, propylparaben

Questions or comments?

Call weekdays 9 AM to 5 PM EST at 1-800-99PrepH or 1-800-997-7374

For most recent product information, visit www.preparationh.com
Pfizer, Madison, NJ 07940 USA © 2011 Pfizer Inc.

PRINCIPAL DISPLAY PANEL

NDC 0573-2883-10

PREPARATION H®

HEMORRHOIDAL SUPPOSITORIES

Reduces Internal Swelling, Soothes and Protects

- Prompt Soothing Relief from Painful Burning, Itching and Discomfort
- Shrinks Swollen Hemorrhoidal Tissue
- Protects Irritated Tissue
- Also for Nighttime Relief

12 SUPPOSITORIES

PRINCIPAL DISPLAY PANEL

NDC 0573-2880-31

PREPARATION H®
HEMORRHOIDAL
SUPPOSITORIES

Provides Relief from
MULTIPLE SYMPTOMS

- Reduces Internal Swelling,
  Soothes & Protects
- Prompt Soothing Relief from
  Painful Burning, Itching and
  Discomfort
- Also for Nighttime Relief

#1 SELLING
#1
HEMORRHOID BRAND

48 SUPPOSITORIES